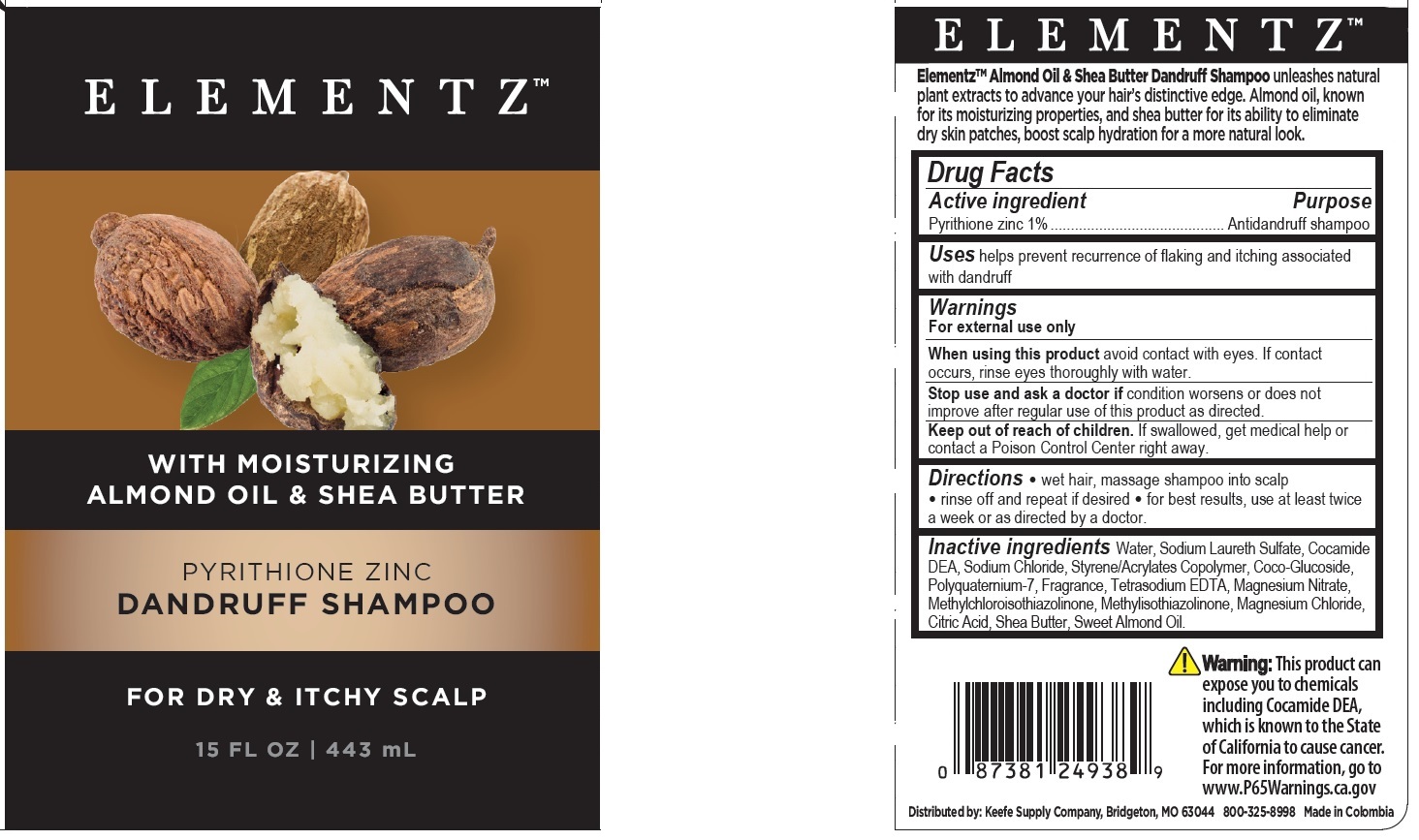 DRUG LABEL: Elementz
NDC: 51870-007 | Form: SHAMPOO
Manufacturer: Keefe Group
Category: otc | Type: HUMAN OTC DRUG LABEL
Date: 20240101

ACTIVE INGREDIENTS: PYRITHIONE ZINC 1 g/100 mL
INACTIVE INGREDIENTS: MAGNESIUM CHLORIDE; CITRIC ACID MONOHYDRATE; STYRENE/ACRYLAMIDE COPOLYMER (MW 500000); COCO GLUCOSIDE; EDETATE SODIUM TETRAHYDRATE; WATER; SODIUM LAURETH SULFATE; COCO DIETHANOLAMIDE; SODIUM CHLORIDE; ALMOND OIL; SHEA BUTTER; METHYLCHLOROISOTHIAZOLINONE; METHYLISOTHIAZOLINONE; POLYQUATERNIUM-7 (70/30 ACRYLAMIDE/DADMAC; 1600 KD); MAGNESIUM NITRATE

Elementz Dandruff Shampoo

Drug Facts

Active ingredient

Pyrithione zinc 1%

Purpose

Antidandruff shampoo

Uses

helps prevent recurrence of flaking and itching associated with dandruff

Warnings

For external use only.

When using this product avoid contact with eyes. If contact occurs, rinse eyes thoroughly with water.

Stop use and ask a doctor if condition worsens or does not improve after regular use of this product as directed.

Keep out of reach of children. If swallowed, get medical help or contact a Poison Control Center right away.

DOSAGE AND ADMINISTRATION

Directions • wet hair, massage shampoo into scalp • rinse and repeat if desired • for maximum dandruff control, use at least twice a week or as directed by a doctor

INACTIVE INGREDIENT

Inactive ingredients Water, Sodium Laureth Sulfate, Cocamide DEA, Sodium Chloride, Styrene/Acrylates Copolymer, Coco-Glucoside, Polyquaternium-7, Fragrance, Tetrasodium EDTA, Magnesium Nitrate, Methylchloroisothiazolinone, Methylisothiazolinone, Magnesium Chloride, Citric Acid, Shea Butter, Sweet Almond Oil.

OTHER SAFETY INFORMATION

Warning: This product can expose you to chemicals including Cocamide DEA, which is known to the State of California to cause cancer. For more information, go to www.P65Warnings.ca.gov

Distributed by:

Keefe Supply Company

Bridgeton, MO 63044

800-325-8998

Made in Colombia

PACKAGE LABEL

ELEMENTZ™

WITH MOISTURIZING ALMOND OIL & SHEA BUTTER

PYRITHIONE ZINC

DANDRUFF SHAMPOO

FOR DRY & ITCHY SCALP

15 FL OZ | 443 mL